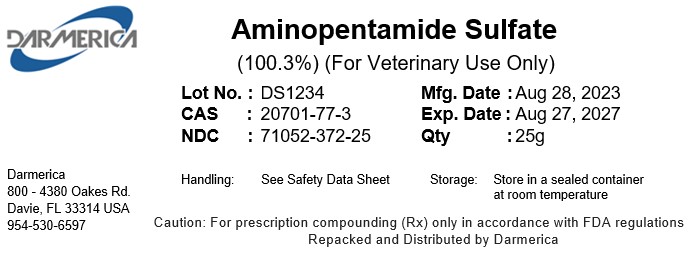 DRUG LABEL: Aminopentamide Sulfate
NDC: 71052-372 | Form: POWDER
Manufacturer: DARMERICA, LLC
Category: other | Type: BULK INGREDIENT - ANIMAL DRUG
Date: 20241219

ACTIVE INGREDIENTS: Aminopentamide Sulfate 1 kg/1 kg

Aminopentamide Sulfate